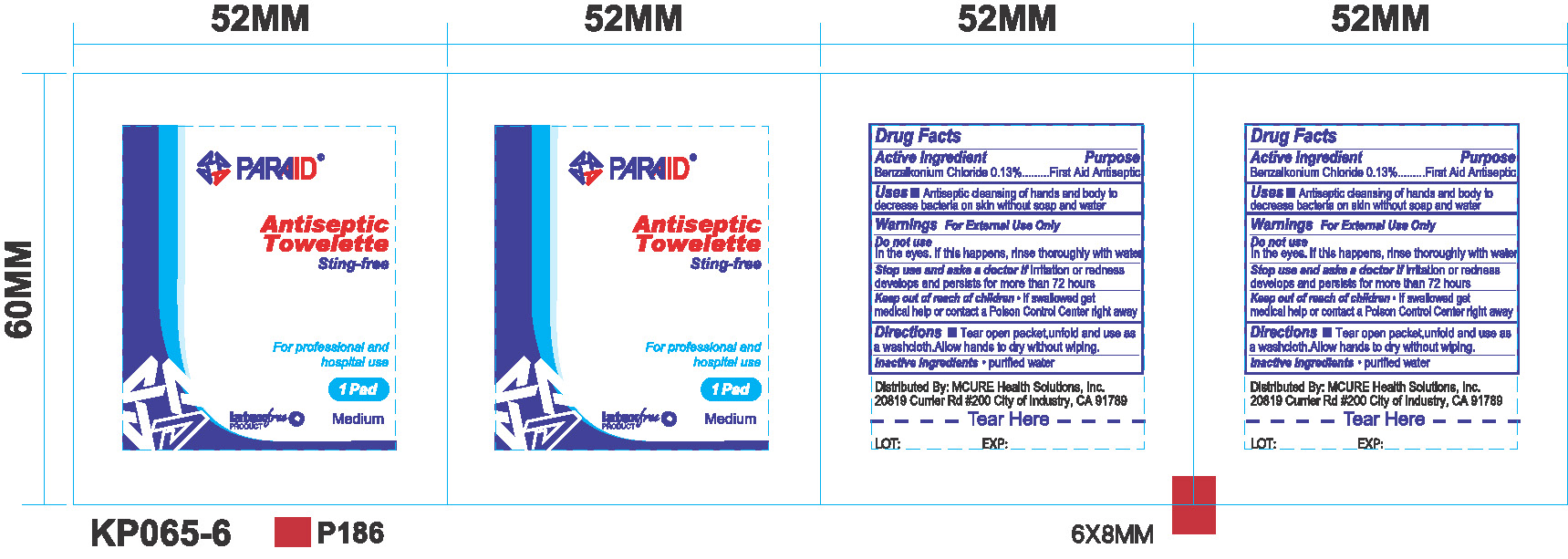 DRUG LABEL: Antiseptic Towelette
NDC: 71310-002 | Form: CLOTH
Manufacturer: Taizhou Kangping Medical Science And Technology Co., Ltd
Category: otc | Type: HUMAN OTC DRUG LABEL
Date: 20170818

ACTIVE INGREDIENTS: BENZALKONIUM CHLORIDE 0.13 g/100 g
INACTIVE INGREDIENTS: WATER

Active ingredient

Purpose - Benzalkonium Chloride 0.13% v/v....................Antiseptic

Uses

For handwashing to decrease bacteria on the skin

Warnings

For external use only.

Do not use

In the eyes. If this happens, rinse thoroughly with water.

Stop use and ask a doctor if irritation or redness develops and persists for more than 72 hours.

Keep out of reach of children. If swallowed, get medical help or contact a Poison Control Center right away.

Directions

- Tear open packet, unfold and use as a washcloth. Allow hands to dry without wiping.

Inactive ingredients

Water

DOSAGE AND ADMINISTRATION

Antiseptic Towelette

Sting-free